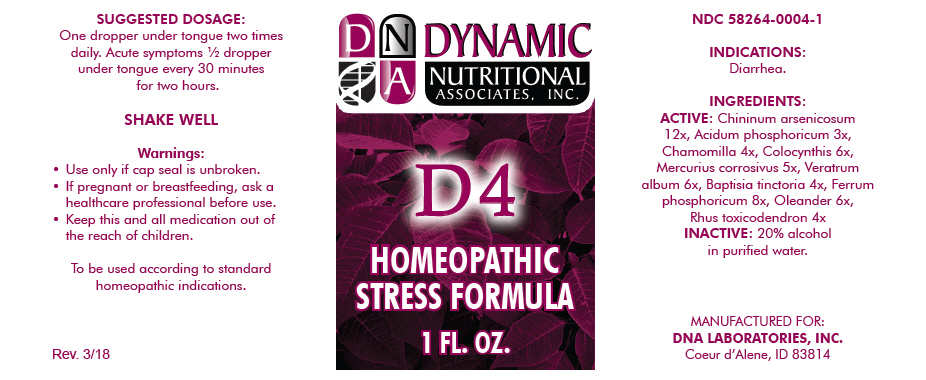 DRUG LABEL: D-4
NDC: 58264-0004 | Form: SOLUTION
Manufacturer: DNA Labs, Inc.
Category: homeopathic | Type: HUMAN OTC DRUG LABEL
Date: 20250113

ACTIVE INGREDIENTS: QUININE ARSENITE 12 [hp_X]/1 mL; PHOSPHORIC ACID 3 [hp_X]/1 mL; MATRICARIA CHAMOMILLA 4 [hp_X]/1 mL; CITRULLUS COLOCYNTHIS FRUIT PULP 6 [hp_X]/1 mL; MERCURIC CHLORIDE 5 [hp_X]/1 mL; VERATRUM ALBUM ROOT 6 [hp_X]/1 mL; BAPTISIA TINCTORIA 4 [hp_X]/1 mL; FERROSOFERRIC PHOSPHATE 8 [hp_X]/1 mL; NERIUM OLEANDER LEAF 6 [hp_X]/1 mL; TOXICODENDRON PUBESCENS LEAF 4 [hp_X]/1 mL
INACTIVE INGREDIENTS: ALCOHOL; WATER

D-4

NDC 58264-0004-1

INDICATIONS

PURPOSE

Diarrhea.

INGREDIENTS

ACTIVE

Chininum arsenicosum 12x, Acidum phosphoricum 3x, Chamomilla 4x, Colocynthis 6x, Mercurius corrosivus 5x, Veratrum album 6x, Baptisia tinctoria 4x, Ferrum phosphoricum 8x, Oleander 6x, Rhus toxicodendron 4x

INACTIVE

20% alcohol in purified water.

SUGGESTED DOSAGE

One dropper under tongue two times daily. Acute symptoms ½ dropper under tongue every 30 minutes for two hours.

STORAGE AND HANDLING

SHAKE WELL

Warnings

- Use only if cap seal is unbroken.

PREGNANCY OR BREAST FEEDING

- If pregnant or breastfeeding, ask a healthcare professional before use.

KEEP OUT OF REACH OF CHILDREN

- Keep this and all medication out of the reach of children.

To be used according to standard homeopathic indications.

PRINCIPAL DISPLAY PANEL - 1 FL. OZ. Bottle Label

DYNAMIC
NUTRITIONAL
ASSOCIATES, INC.

D 4

HOMEOPATHIC
STRESS FORMULA

1 FL. OZ.